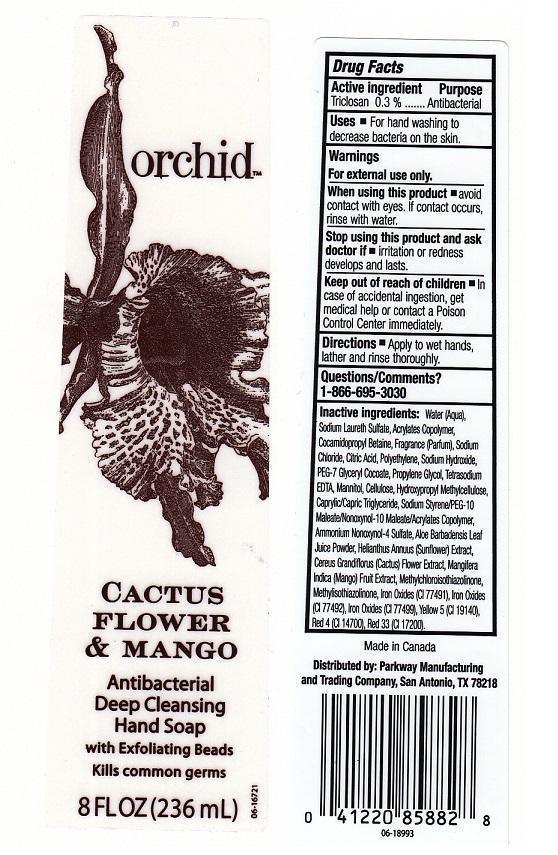 DRUG LABEL: ORCHID
NDC: 37808-091 | Form: LIQUID
Manufacturer: H.E.B.
Category: otc | Type: HUMAN OTC DRUG LABEL
Date: 20130813

ACTIVE INGREDIENTS: TRICLOSAN 3 mg/1 mL
INACTIVE INGREDIENTS: WATER; SODIUM LAURETH SULFATE; METHACRYLIC ACID - METHYL METHACRYLATE COPOLYMER (1:1); COCAMIDOPROPYL BETAINE; SODIUM CHLORIDE; CITRIC ACID MONOHYDRATE; HIGH DENSITY POLYETHYLENE; SODIUM HYDROXIDE; PEG-7 GLYCERYL COCOATE; PROPYLENE GLYCOL; EDETATE SODIUM; MANNITOL; POWDERED CELLULOSE; HYPROMELLOSES; MEDIUM-CHAIN TRIGLYCERIDES; AMMONIUM NONOXYNOL-4 SULFATE; ALOE VERA LEAF; HELIANTHUS ANNUUS FLOWERING TOP; SELENICEREUS GRANDIFLORUS FLOWER; MANGO; METHYLCHLOROISOTHIAZOLINONE; METHYLISOTHIAZOLINONE; FERRIC OXIDE RED; FERRIC OXIDE YELLOW; FERROSOFERRIC OXIDE; FD&C YELLOW NO. 5; FD&C RED NO. 4; D&C RED NO. 33

DRUG FACTS

ACTIVE INGREDIENT

TRICLOSAN 0.3%

PURPOSE

ANTIBACTERIAL

USES

FOR HAND WASHING TO DECREASE BACTERIA ON THE SKIN.

WARNINGS

FOR EXTERNAL USE ONLY.

WHEN USING THIS PRODUCT

AVOID CONTACT WITH EYES. IF CONTACT OCCURS, RINSE WITH WATER.

STOP USING THIS PRODUCT AND ASK DOCTOR IF

IRRITATION OR REDNESS DEVELOPS AND LASTS.

KEEP OUT OF REACH OF CHILDREN

IN CASE OF ACCIDENTAL INGESTION, GET MEDICAL HELP OR CONTACT A POISON CONTROL CENTER IMMEDIATELY.

DIRECTIONS

APPLY TO WET HANDS, LATHER AND RINSE THOROUGHLY.

QUESTIONS/COMMENTS?

1-866-695-3030

INACTIVE INGREDIENTS:

WATER (AQUA), SODIUM LAURETH SULFATE, ACRYLATES COPOLYMER, COCAMIDOPROPYL BETAINE, FRAGRANCE (PARFUM), SODIUM CHLORIDE, CITRIC ACID, POLYETHYLENE, SODIUM HYDROXIDE, PEG-7 GYCERYL COCOATE, PROPYLENE GLYCOL, TETRASODIUM EDTA, MANNITOL, CELLUOSE, HYDROXYPROPYL METHYLCELLULOSE, CAPRYLIC/CAPRIC TRIGLYCERIDE, SODIUM STYRENE/PEG-10 MALEATE/NONOXYNOL-10 MALEATE/ACRYLATES COPOLYMER, AMMONIUM NONOXYNOL-4 SULFATE, ALOE BARBADENSIS LEAF JUICE POWDER, HELIANTHUS ANNUUS (SUNFLOWER) EXTRACT, CEREUS GRANDIFLORUS (CACTUS) FLOWER EXTRACT, MANGIFERA INDICA (MANGO) FRUIT EXTRACT, METHYLCHLOROISOTHIAZOLINONE, METHYLISOTHIAZOLINONE, IRON OXIDES (CI 77491), IRON OXIDES (CI 77492), IRON OXIDES (CI 77499), YELLOW 5 (CI 19140), RED 4 (CI 14700), RED 33 (CI 17200).